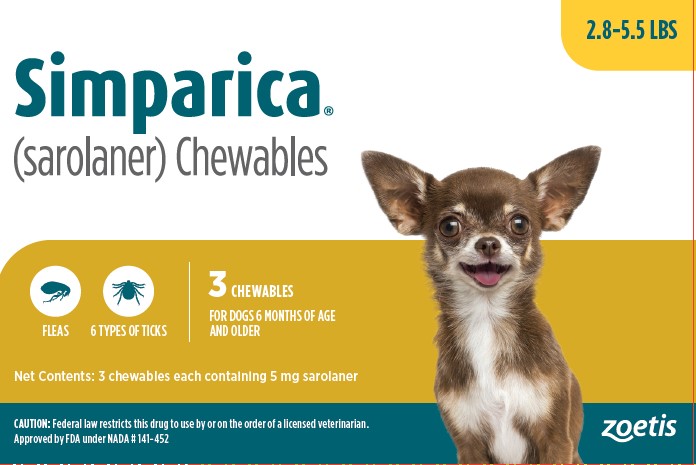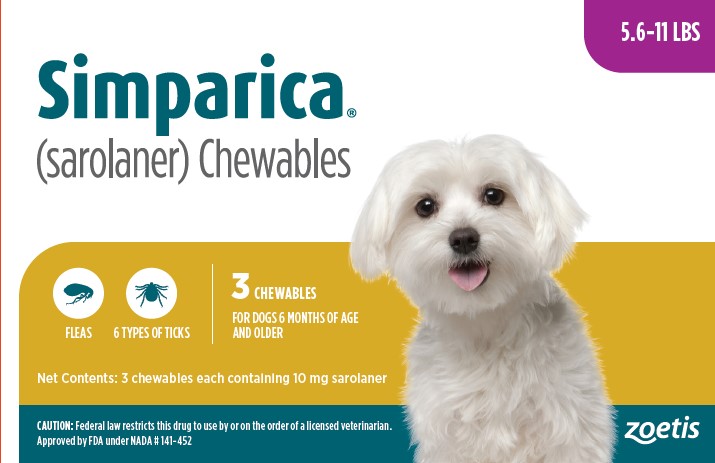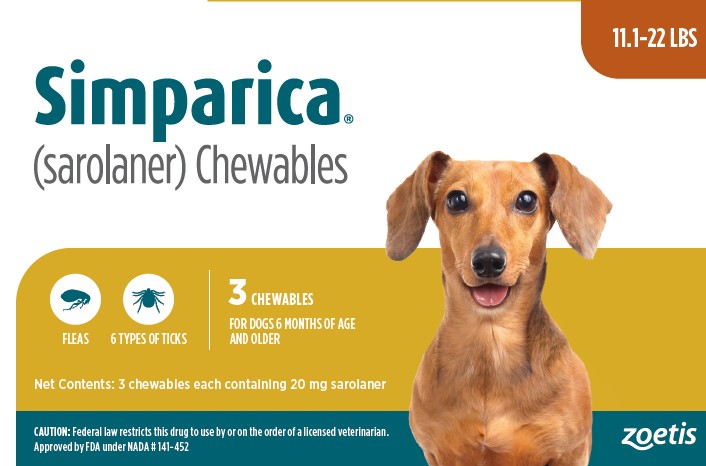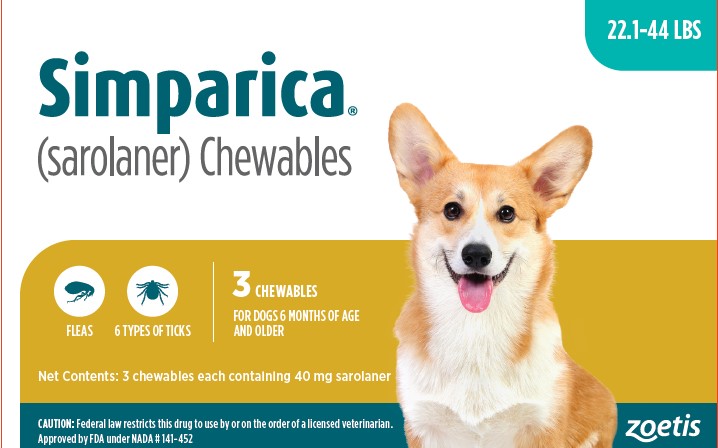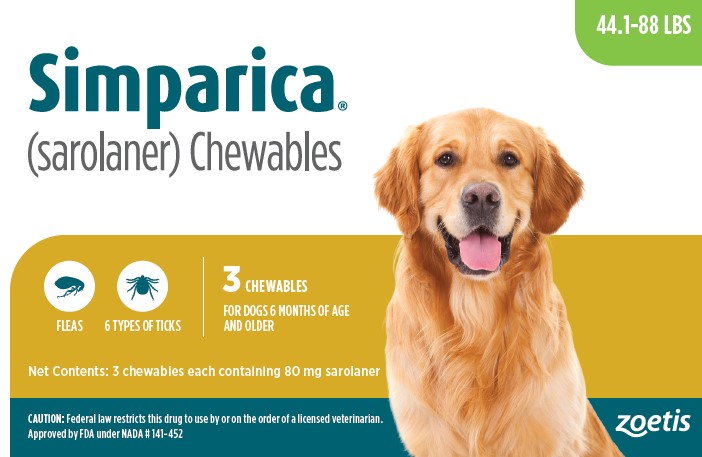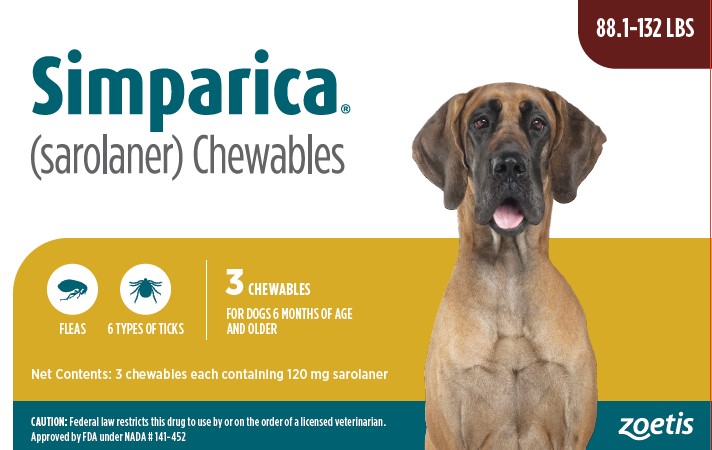 DRUG LABEL: Simparica Chewables
NDC: 54771-2015 | Form: TABLET, CHEWABLE
Manufacturer: Zoetis Inc.
Category: animal | Type: PRESCRIPTION ANIMAL DRUG LABEL
Date: 20241203

ACTIVE INGREDIENTS: SAROLANER 5 mg/1 1

Simparica®

Simparica®

(sarolaner) Chewables

FOR ORAL USE IN DOGS ONLY

CAUTION

Federal law restricts this drug to use by or on the order of a licensed veterinarian.

Description

SIMPARICA is a flavored, chewable tablet for administration to dogs over 6 months of age according to their weight. Each tablet is formulated to provide a minimum sarolaner dosage of 0.91 mg/lb (2 mg/kg) body weight.

Sarolaner is a member of the isoxazoline class of parasiticides and the chemical name is 1-(5'-((5S)-5-(3,5-Dichloro-4-fluorophenyl)-5-(trifluoromethyl)-4,5-dihydroisoxazol-3-yl)-3'-H-spiro(azetidine-3,1'-(2)benzofuran)-1-yl)-2-(methylsulfonyl)ethanone. SIMPARICA contains the S-enantiomer of sarolaner.

Indications

SIMPARICA kills adult fleas, and is indicated for the treatment and prevention of flea infestations (Ctenocephalides felis), and the treatment and control of tick infestations [Amblyomma americanum (lone star tick), Amblyomma maculatum (Gulf Coast tick), Dermacentorvariabilis (American dog tick), Ixodes scapularis (black-legged tick), Rhipicephalus sanguineus (brown dog tick), and Haemaphysalis longicornis (Asian longhorned tick)] for one month in dogs 6 months of age or older and weighing 2.8 pounds or greater. SIMPARICA is indicated for the prevention of Borrelia burgdorferi infections as a direct result of killing lxodes scapularis vector ticks.

Dosage and Administration

SIMPARICA is given orally once a month at the recommended minimum dosage of 0.91 mg/lb (2 mg/kg).

Dosage Schedule:

Body Weight | SAROLANER per Tablet (mg) | Number of Tablets Administered
2.8 to 5.5 lbs | 5 | One
5.6 to 11 lbs | 10 | One
11.1 to 22 lbs | 20 | One
22.1 to 44 lbs | 40 | One
44.1 to 88 lbs | 80 | One
88.1 to 132 lbs | 120 | One
>132.1 lbs | Administer the appropriate combination of tablets

SIMPARICA can be offered by hand, in the food, or administered like other tablet medications.

Care should be taken that the dog consumes the complete dose, and treated animals should be observed for a few minutes to ensure that part of the dose is not lost or refused. If a dose is missed, administer SIMPARICA and resume a monthly dosing schedule.

SIMPARICA should be administered at monthly intervals.

Flea Treatment and Prevention:

Treatment with SIMPARICA may begin at any time of the year. In areas where fleas are common year-round, monthly treatment with SIMPARICA can continue the entire year without interruption.

To minimize the likelihood of flea re-infestation, it is important to treat all dogs and cats within a household with an approved flea control product.

Tick Treatment and Control:

Treatment with SIMPARICA can begin at any time of the year (see Effectiveness).

Contraindications

There are no known contraindications for the use of SIMPARICA.

Warnings

Not for use in humans. Keep this and all drugs out of reach of children. For use in dogs only. Do not use SIMPARICA in cats.
SIMPARICA should not be used in dogs less than 6 months of age (see Animal Safety).
Keep SIMPARICA in a secure location out of reach of dogs, cats and other animals to prevent accidental ingestion or overdose.

Precautions

Sarolaner is a member of the isoxazoline class. This class has been associated with neurologic adverse reactions including tremors, ataxia, and seizures. Seizures have been reported in dogs receiving isoxazoline class drugs, even in dogs without a history of seizures. Use with caution in dogs with a history of seizures or neurologic disorders.
The safe use of SIMPARICA has not been evaluated in breeding, pregnant, or lactating dogs.

Adverse Reactions

SIMPARICA was administered in a well-controlled US field study, which included a total of 479 dogs (315 dogs treated with SIMPARICA and 164 dogs treated with active control once monthly for three treatments).
Over the 90-day study period, all observations of potential adverse reactions were recorded.

Table 1. Dogs with adverse reactions
Adverse reaction | sarolaner | sarolaner | active control | active control
 | N | % (n = 315) | N | # (n =164)
Vomiting | 3 | 0.95% | 9 | 5.50%
Diarrhea | 2 | 0.63% | 2 | 1.20%
Lethargy | 1 | 0.32% | 2 | 1.20%
Inappetence | 0 | 0% | 3 | 1.80%

Additionally, one female dog aged 8.6 years exhibited lethargy, ataxia while posturing to eliminate, elevated third eyelids, and inappetence one day after receiving SIMPARICA concurrently with a heartworm preventative (ivermectin/pyrantel pamoate). The signs resolved one day later. After the day 14 visit, the owner elected to withdraw the dog from the study.
Abnormal neurologic signs such as tremors, decreased conscious proprioception, ataxia, decreased or absent menace, and/or seizures were reported in dogs receiving SIMPARICA (see Animal Safety).
Post Approval Experience (2019):
The following adverse events are based on post-approval adverse drug experience reporting for SIMPARICA. Not all adverse events are reported to FDA CVM. It is not always possible to reliably estimate the adverse event frequency or establish a causal relationship to product exposure using these data.
The following adverse events reported for dogs are listed in decreasing order of reporting frequency:
Vomiting, tremors, lethargy, seizure, diarrhea (with and without blood), anorexia, ataxia, pruritus, hypersalivation and hyperactivity.

Contact Information

For a copy of the Safety Data Sheet (SDS) or to report adverse reactions call Zoetis Inc. at 1-888-963-8471. Additional information can be found at www.SIMPARICA.com. For additional information about adverse drug experience reporting for animal drugs, contact FDA at 1-888-FDA-VETS or www.fda.gov/reportanimalae.

Clinical Pharmacology

Sarolaner is rapidly and well absorbed following oral administration of SIMPARICA. In a study of 12 Beagle dogs the mean maximum plasma concentration (Cmax) was 1100 ng/mL and the mean time to maximum concentration (Tmax) occurred at 3 hours following a single oral dose of 2 mg/kg to fasted animals. The mean oral bioavailability was 86% and 107% in fasted and fed dogs, respectively. The mean oral T1/2 values for fasted and fed animals was 10 and 12 days respectively.

Sarolaner is distributed widely; the mean volume of distribution (Vdss) was 2.81 L/kg bodyweight following a 2 mg/kg intravenous dose of sarolaner. Sarolaner is highly bound (≥99.9%) to plasma proteins. The metabolism of sarolaner appears to be minimal in the dog. The primary route of sarolaner elimination from dogs is biliary excretion with elimination via the feces.

Following repeat administration of SIMPARICA once every 28 days for 10 doses to Beagle dogs at 1X, 3X, and 5X the maximum intended clinical dose of 4 mg/kg, steady-state plasma concentrations were reached after the 6th dose. Following treatment at 1X, 3X, and 5X the maximum intended clinical dose of 4 mg/kg, sarolaner systemic exposure was dose proportional over the range 1X to 5X.

Mode of Action

The active substance of SIMPARICA, sarolaner, is an acaricide and insecticide belonging to the isoxazoline group. Sarolaner inhibits the function of the neurotransmitter gammaaminobutyric acid (GABA) receptor and glutamate receptor, and works at the neuromuscular junction in insects. This results in uncontrolled neuromuscular activity leading to death in insects or acarines.

Effectiveness

In a well-controlled laboratory study, SIMPARICA began to kill fleas 3 hours after initial administration and reduced the number of live fleas by ≥96.2% within 8 hours after flea infestation through Day 35.

In a separate well-controlled laboratory study, SIMPARICA demonstrated 100% effectiveness against adult fleas within 24 hours following treatment and maintained 100% effectiveness against weekly re-infestations for 35 days.

In a study to explore flea egg production and viability, SIMPARICA killed fleas before they could lay eggs for 35 days. In a study to simulate a flea-infested home environment, with flea infestations established prior to the start of treatment and re-infestations on Days 7, 37 and 67, SIMPARICA administered monthly for three months demonstrated >95.6% reduction in adult fleas within 14 days after treatment and reached 100% on Day 60.

In well-controlled laboratory studies, SIMPARICA demonstrated ≥99% effectiveness against an initial infestation of Amblyomma americanum, Amblyomma maculatum, Dermacentor variabilis, Ixodes scapularis, Rhipicephalus sanguineus, and Haemaphysalis longicornis 48 hours post-administration and maintained >96% effectiveness 48 hours post re-infestation for 30 days. In two separate, well-controlled laboratory studies, SIMPARICA was effective at preventing Borrelia burgdorferi infections after dogs were infested with lxodes scapularis vector ticks 28 days post-treatment.

In a well-controlled 90-day US field study conducted in households with existing flea infestations of varying severity, the effectiveness of SIMPARICA against fleas on Day 30, 60 and 90 visits compared to baseline was 99.4%, 99.8%, and 100%, respectively. Dogs with signs of flea allergy dermatitis showed improvement in erythema, papules, scaling, alopecia, dermatitis/pyodermatitis and pruritus as a direct result of eliminating fleas.

Animal Safety

In a margin of safety study, SIMPARICA was administered orally to 8-week-old Beagle puppies at doses of 0, 1X, 3X, and 5X the maximum recommended dose (4 mg/kg) at 28-day intervals for 10 doses (8 dogs per group). The control group received placebo tablets. No neurologic signs were observed in the 1X group. In the3X group, one male dog exhibited tremors and ataxia post-dose on Day 0; one female dog exhibited tremors on Days 1, 2, 3, and 5; and one female dog exhibited tremors on Day 1. In the 5X group, one female dog had a seizure on Day 61 (5 days after third dose); one female dog had tremors post-dose on Day 0 and abnormal head coordination after dosing on Day 140; and one female dog exhibited seizures associated with the second and fourth doses and tremors associated with the second and third doses. All dogs recovered without treatment. Except for the observation of abnormal head coordination in one dog in the 5X group two hours after dosing on Day 140 (dose 6). There were no treatment-related neurological signs observed once the dogs reached the age of 6 months.

In a separate exploratory pharmacokinetic study, one female dog dosed at 12 mg/kg (3X the maximum recommended dose) exhibited lethargy, anorexia, and multiple neurological signs including ataxia, tremors, disorientation, hypersalivation, diminished proprioception, and absent menace, approximately 2 days after a third monthly dose. The dog was not treated, and was ultimately euthanized. The first two doses resulted in plasma concentrations that were consistent with those of the other dogs in the treatment group. Starting at 7 hours after the third dose, there was a rapid 2.5 fold increase in plasma concentrations within 41 hours, resulting in a Cmax more than 7-fold higher than the mean Cmax at the maximum recommended use dose. No cause for the sudden increase in sarolaner plasma concentrations was identified.

Storage Information

Store at or below 30°C (86°F) with excursions permitted up to 40°C (104°F).

How Supplied

SIMPARICA (sarolaner) Chewables are available in six flavored tablet sizes: 5, 10, 20, 40, 80, and 120 mg. Each tablet size is available in color-coded packages of one, three, or six tablets.

Approved by FDA under NADA # 141-452
zoetis
Distributed by:
Zoetis Inc.
Kalamazoo, MI 49007

Revised: May 2024
40046623

PRINCIPAL DISPLAY PANEL 5 mg Carton

40046565

PRINCIPAL DISPLAY PANEL 10 mg Carton

40046566

PRINICIPAL DISPLAY PANEL 20 mg Carton

40046604

PRINCIPAL DISPLAY PANEL 40 mg Carton

40046606

PRINCIPAL DISPLAY PANEL 80 mg Carton

40046608

PRINCIPAL DISPLAY PANEL 120 mg Carton

40046610